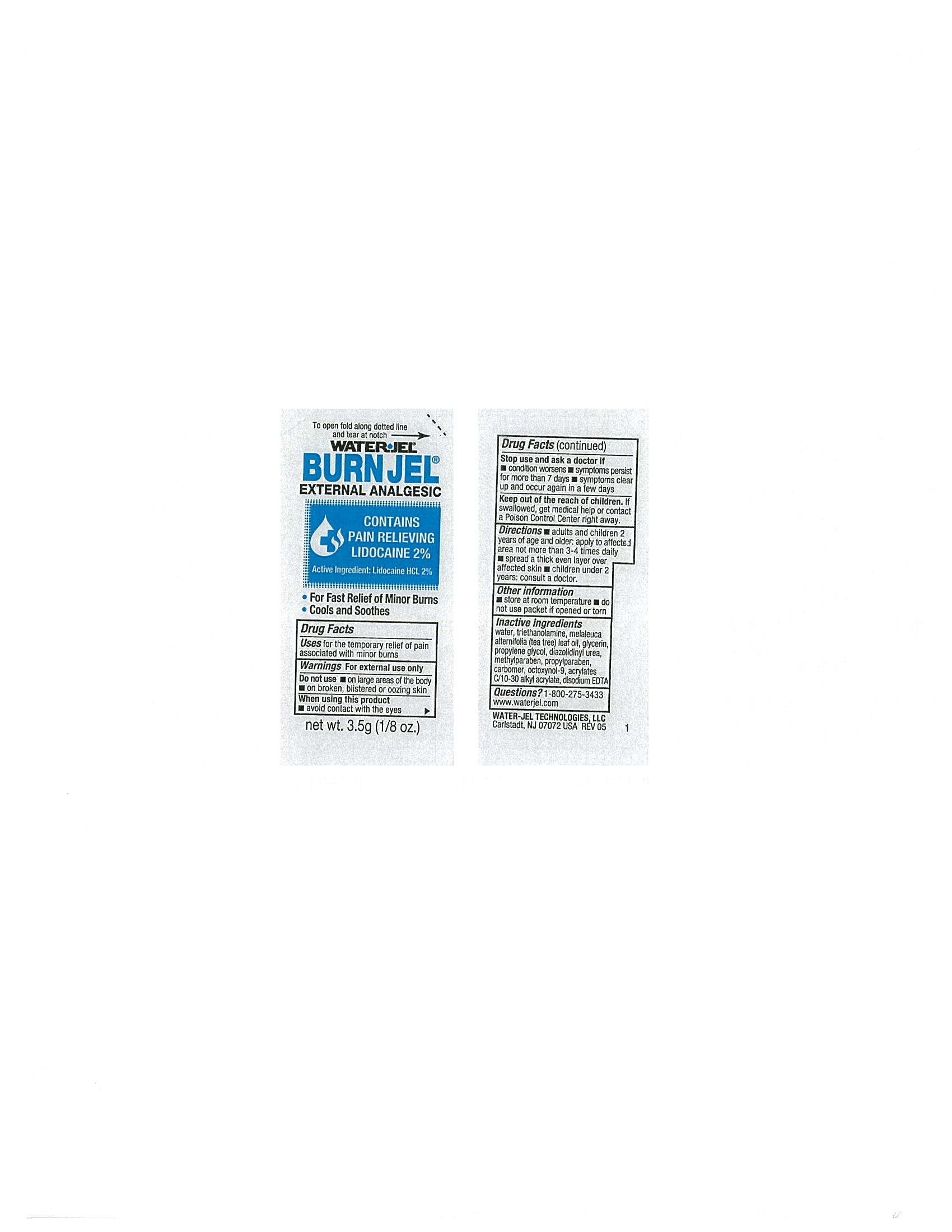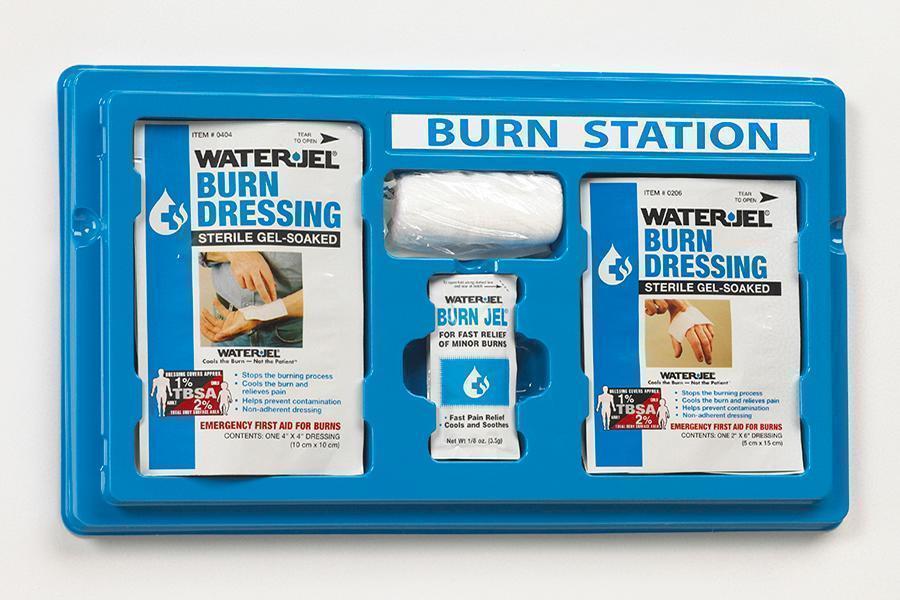 DRUG LABEL: EBSS-5
NDC: 59898-160 | Form: KIT | Route: TOPICAL
Manufacturer: Water-Jel Technologies
Category: otc | Type: HUMAN OTC DRUG LABEL
Date: 20171207

ACTIVE INGREDIENTS: LIDOCAINE HYDROCHLORIDE 2 g/100 mL
INACTIVE INGREDIENTS: CARBOMER HOMOPOLYMER TYPE C; GLYCERIN; PROPYLENE GLYCOL; METHYLPARABEN; TEA TREE OIL; DIAZOLIDINYL UREA; TROLAMINE; OCTOXYNOL-9; CARBOMER HOMOPOLYMER TYPE B; PROPYLPARABEN; EDETATE DISODIUM

EBSS-5

Active ingredient

Lidocaine HCl 2.0 %

Purpose

External analgesic

Uses

for the temporary relief of pain associated with minor burns

Warnings

For external use only

Do not use

on large areas of the body

on broken, blistered or oozing skin

When using this product

- avoid contact with eyes

Stop use and ask a doctor if

- conditions worsens
- symptoms persist for more than 7 days
- symptoms clears up and occur again in a few days

Keep out of the reach of children

If swallowed, get medical help or contact a Poison Control Center right away.

Directions

- adults and children 2 years of age and older; apply to affected area not more than 3 to 4 times daily
- spread a thick even layer over affected skin
- children under 2 years of age: consult a doctor

Other information

- store at room temperature
- do not use packeet if opened or torn
- you may report a serious adverse reaction to this product to 800-275-3433

Inactive ingredients

triethanolamine, meleleuca alternifolia (tea tree) leaf oil, glycerin, propylene glycol, diazolidinyl urea, methylparaben, propylparaben, carbomer, octoxynol-9, acrylates C/10-30 alkyl acrylate, disodium EDTA

Questions

1-800-275-3433 www.waterjel.com

MEDICAL DEVICES
2 | 2" x 6" Burn Dressings
2 | 4" x 4" Burn Dressings
1 | 3" Roll of Gauze